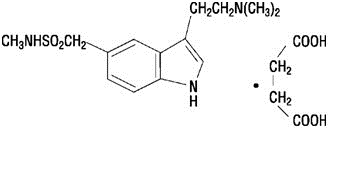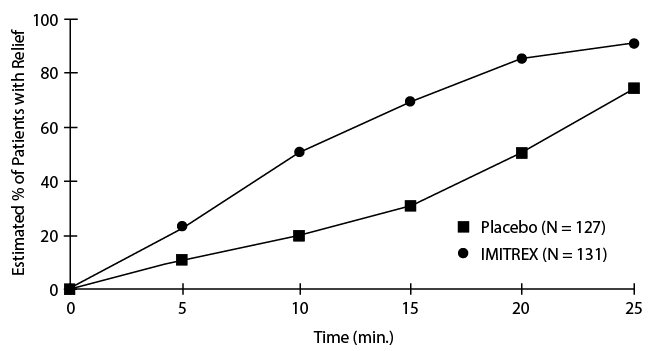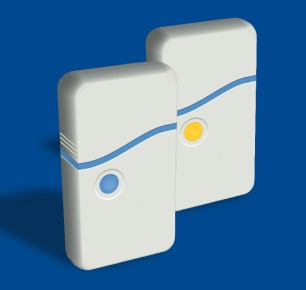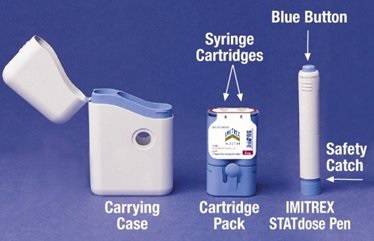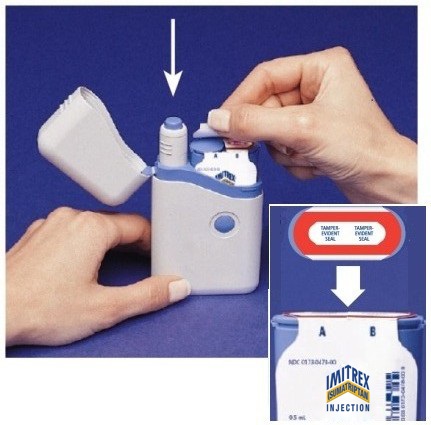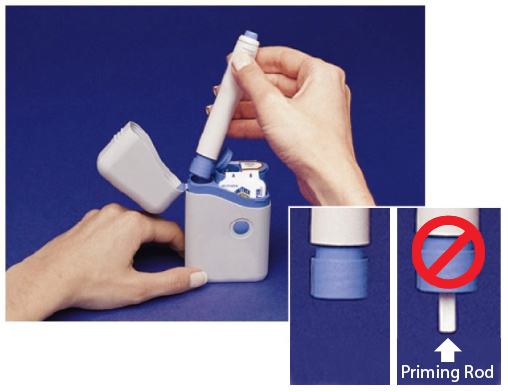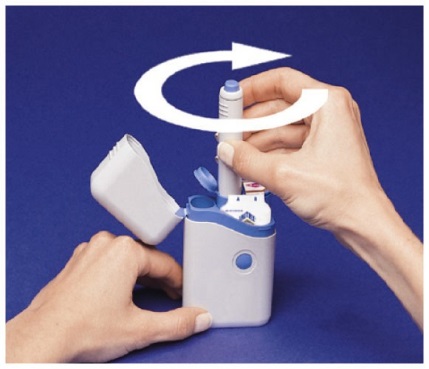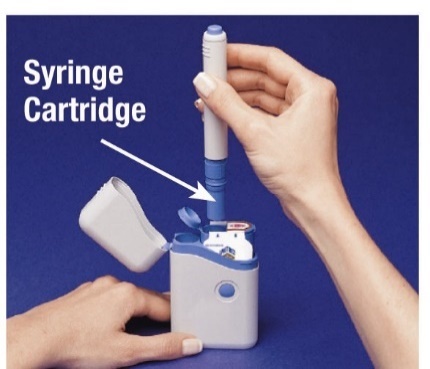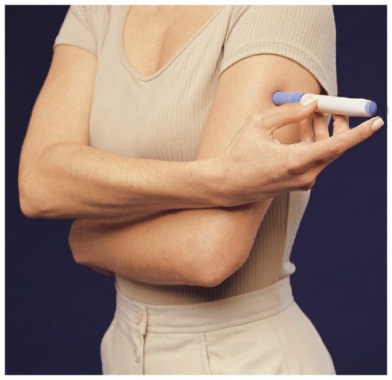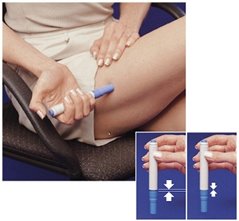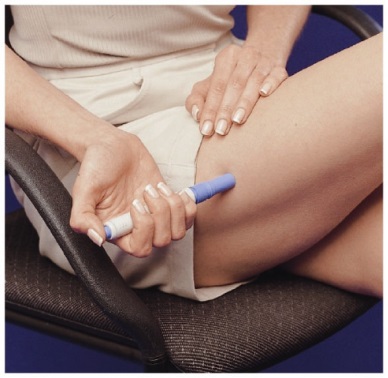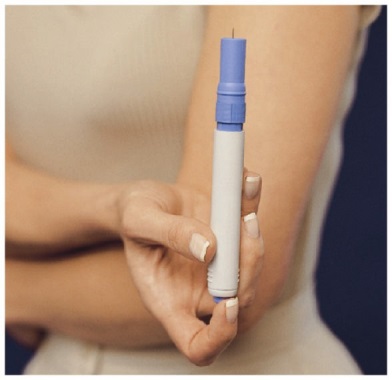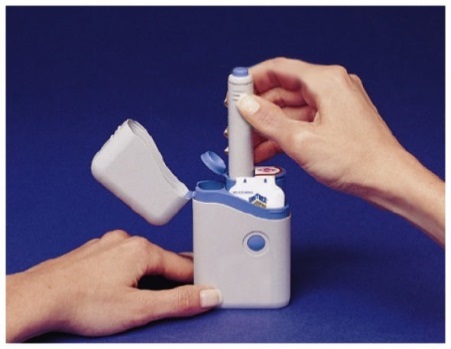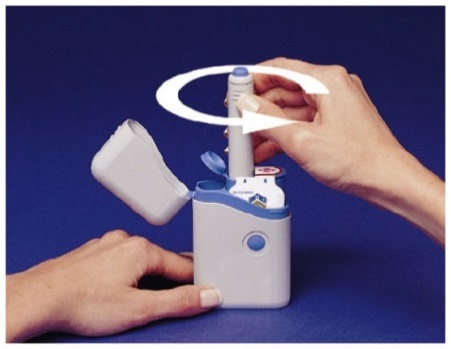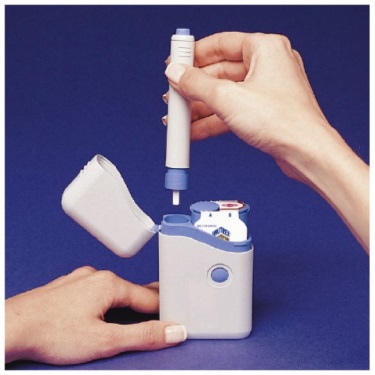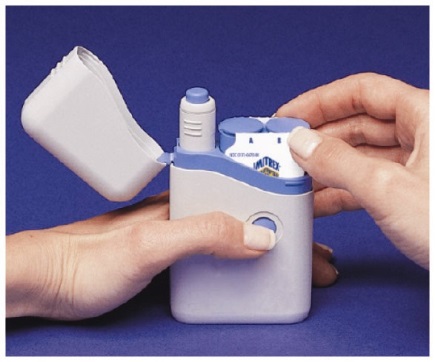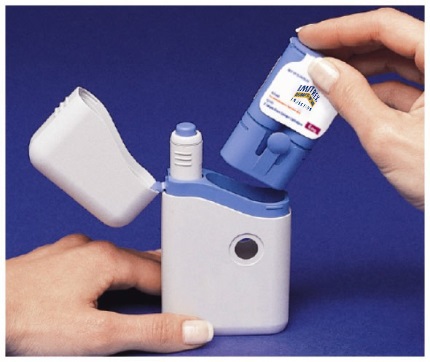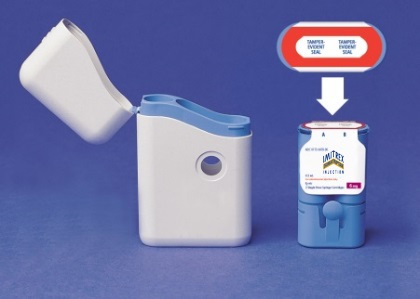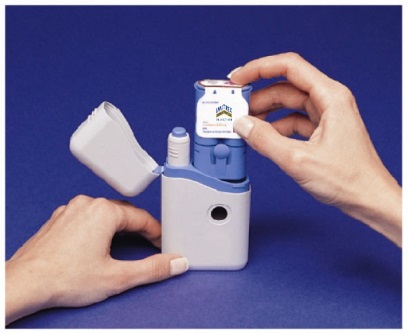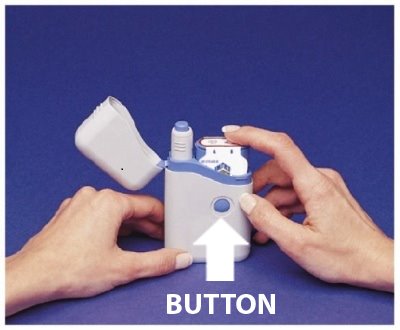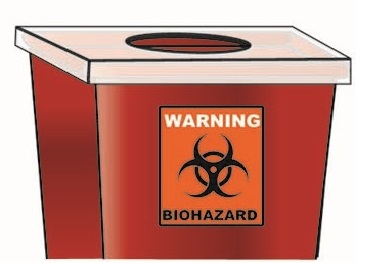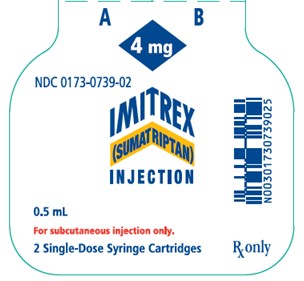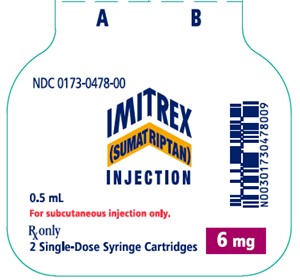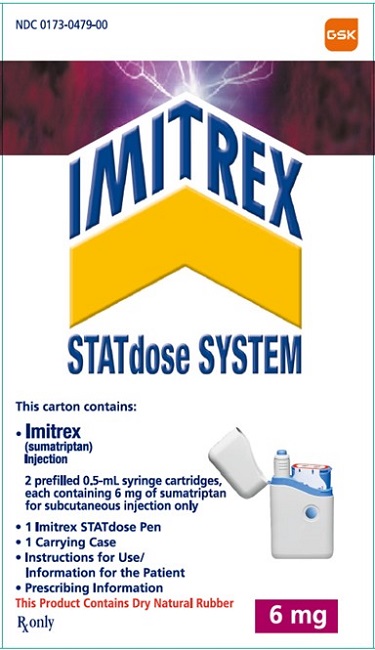 DRUG LABEL: IMITREX
NDC: 0173-0739 | Form: INJECTION
Manufacturer: GlaxoSmithKline LLC
Category: prescription | Type: HUMAN PRESCRIPTION DRUG LABEL
Date: 20251209

ACTIVE INGREDIENTS: SUMATRIPTAN SUCCINATE 4 mg/0.5 mL
INACTIVE INGREDIENTS: SODIUM CHLORIDE 3.8 mg/0.5 mL; WATER

HIGHLIGHTS OF PRESCRIBING INFORMATION

These highlights do not include all the information needed to use IMITREX safely and effectively. See full prescribing information for IMITREX.
IMITREX (sumatriptan) injection, for subcutaneous use
Initial U.S. Approval: 1992

1 INDICATIONS AND USAGE

IMITREX injection is a serotonin (5-HT1B/1D) receptor agonist (triptan) indicated for:

- Acute treatment of migraine with or without aura in adults. (1)
- Acute treatment of cluster headache in adults. (1)

Limitations of Use

- Use only if a clear diagnosis of migraine or cluster headache has been established. (1)
- Not indicated for the prophylactic therapy of migraine or cluster headache attacks. (1)

2 DOSAGE AND ADMINISTRATION

- For subcutaneous use only. (2.1)
- Acute treatment of migraine: single dose of 4 mg or 6 mg. (2.1)
- Acute treatment of cluster headache: single dose of 6 mg. (2.1)
- Maximum dose in a 24-hour period: 12 mg, separate doses by at least 1 hour. (2.1)
- The needle shield of the prefilled syringe contains dry natural rubber (a latex derivative) which may cause allergic reactions in latex-sensitive patients. (2.2)

3 DOSAGE FORMS AND STRENGTHS

Injection: 4- and 6-mg single-dose prefilled syringe cartridges for use with IMITREX STATdose Pen. (3)

4 CONTRAINDICATIONS

- History of coronary artery disease or coronary artery vasospasm. (4)
- Wolff-Parkinson-White syndrome or other cardiac accessory conduction pathway disorders. (4)
- History of stroke, transient ischemic attack, or hemiplegic or basilar migraine. (4)
- Peripheral vascular disease. (4)
- Ischemic bowel disease. (4)
- Uncontrolled hypertension. (4)
- Recent (within 24 hours) use of another 5-HT1 agonist (e.g., another triptan) or of an ergotamine-containing medication. (4)
- Concurrent or recent (past 2 weeks) use of monoamine oxidase-A inhibitor. (4)
- Hypersensitivity to IMITREX (angioedema and anaphylaxis seen). (4)
- Severe hepatic impairment. (4)

5 WARNINGS AND PRECAUTIONS

- Myocardial ischemia/infarction and Prinzmetal’s angina: Perform cardiac evaluation in patients with multiple cardiovascular risk factors. (5.1)
- Arrhythmias: Discontinue IMITREX if occurs. (5.2)
- Chest/throat/neck/jaw pain, tightness, pressure, or heaviness: Generally not associated with myocardial ischemia; evaluate for coronary artery disease in patients at high risk. (5.3)
- Cerebral hemorrhage, subarachnoid hemorrhage, and stroke: Discontinue IMITREX if occurs. (5.4)
- Gastrointestinal ischemic reactions and peripheral vasospastic reactions: Discontinue IMITREX if occurs. (5.5)
- Medication overuse headache: Detoxification may be necessary. (5.6)
- Serotonin syndrome: Discontinue IMITREX if occurs. (5.7)
- Seizures: Use with caution in patients with epilepsy or a lowered seizure threshold. (5.10)

6 ADVERSE REACTIONS

Most common adverse reactions (≥5% and >placebo) were injection site reactions, tingling, dizziness/vertigo, warm/hot sensation, burning sensation, feeling of heaviness, pressure sensation, flushing, feeling of tightness, and numbness. (6.1)

To report SUSPECTED ADVERSE REACTIONS, contact GlaxoSmithKline at 1-888-825-5249 or FDA at 1-800-FDA-1088 or www.fda.gov/medwatch.

8 USE IN SPECIFIC POPULATIONS

Pregnancy: Based on animal data, may cause fetal harm. (8.1)

FULL PRESCRIBING INFORMATION

1 INDICATIONS AND USAGE

IMITREX injection is indicated in adults for (1) the acute treatment of migraine, with or without aura, and (2) the acute treatment of cluster headache.

Limitations of Use

- Use only if a clear diagnosis of migraine or cluster headache has been established. If a patient has no response to the first migraine or cluster headache attack treated with IMITREX injection, reconsider the diagnosis before IMITREX injection is administered to treat any subsequent attacks.
- IMITREX injection is not indicated for the prevention of migraine or cluster headache attacks.

2 DOSAGE AND ADMINISTRATION

2.1 Dosing Information

The maximum single recommended adult dose of IMITREX injection for the acute treatment of migraine or cluster headache is 6 mg injected subcutaneously. For the treatment of migraine, if side effects are dose limiting, the lower dose of 4 mg may be used [see Clinical Studies (14.1)]. For the treatment of cluster headache, the efficacy of lower doses has not been established.

The maximum cumulative dose that may be given in 24 hours is 12 mg, two 6-mg injections separated by at least 1 hour. A second 6-mg dose should only be considered if some response to a first injection was observed.

2.2 Administration Using the IMITREX STATdose Pen

An autoinjector device (IMITREX STATdose Pen) is available for use with 4-mg and 6-mg prefilled syringe cartridges. With this device, the needle penetrates approximately 1/4 inch (5 to 6 mm). The injection is intended to be given subcutaneously, and intramuscular or intravascular delivery must be avoided. Instruct patients on the proper use of IMITREX STATdose Pen and direct them to use injection sites with an adequate skin and subcutaneous thickness to accommodate the length of the needle.

The needle shield of the prefilled syringe contains dry natural rubber (a latex derivative) [see Warnings and Precautions (5.9)].

3 DOSAGE FORMS AND STRENGTHS

Injection: 4-mg and 6-mg single-dose prefilled syringe cartridges for use with the IMITREX STATdose Pen. Each 0.5 mL injection contains 5.6 mg or 8.4 mg of sumatriptan succinate equivalent to 4 mg or 6 mg of sumatriptan, respectively.

4 CONTRAINDICATIONS

IMITREX injection is contraindicated in patients with:

- Ischemic coronary artery disease (CAD) (angina pectoris, history of myocardial infarction, or documented silent ischemia) or coronary artery vasospasm, including Prinzmetal’s angina [see Warnings and Precautions (5.1)].
- Wolff-Parkinson-White syndrome or arrhythmias associated with other cardiac accessory conduction pathway disorders [see Warnings and Precautions (5.2)].
- History of stroke or transient ischemic attack (TIA) or history of hemiplegic or basilar migraine because these patients are at a higher risk of stroke [see Warnings and Precautions (5.4)].
- Peripheral vascular disease [see Warnings and Precautions (5.5)].
- Ischemic bowel disease [see Warnings and Precautions (5.5)].
- Uncontrolled hypertension [see Warnings and Precautions (5.8)].
- Recent use (i.e., within 24 hours) of ergotamine-containing medication, ergot-type medication (such as dihydroergotamine or methysergide), or another 5-hydroxytryptamine1 (5-HT1) agonist [see Drug Interactions (7.1, 7.3)].
- Concurrent administration of a monoamine oxidase (MAO)-A inhibitor or recent (within 2 weeks) use of an MAO-A inhibitor [see Drug Interactions (7.2), Clinical Pharmacology (12.3)].
- Hypersensitivity to IMITREX (angioedema and anaphylaxis seen) [see Warnings and Precautions (5.9)].
- Severe hepatic impairment [see Clinical Pharmacology (12.3)].

5 WARNINGS AND PRECAUTIONS

5.1 Myocardial Ischemia, Myocardial Infarction, and Prinzmetal’s Angina

The use of IMITREX injection is contraindicated in patients with ischemic or vasospastic CAD. There have been rare reports of serious cardiac adverse reactions, including acute myocardial infarction, occurring within a few hours following administration of IMITREX injection. Some of these reactions occurred in patients without known CAD. IMITREX injection may cause coronary artery vasospasm (Prinzmetal’s angina), even in patients without a history of CAD.

Perform a cardiovascular evaluation in triptan-naive patients who have multiple cardiovascular risk factors (e.g., increased age, diabetes, hypertension, smoking, obesity, strong family history of CAD) prior to receiving IMITREX injection. If there is evidence of CAD or coronary artery vasospasm, IMITREX injection is contraindicated. For patients with multiple cardiovascular risk factors who have a negative cardiovascular evaluation, consider administering the first dose of IMITREX injection in a medically supervised setting and performing an electrocardiogram (ECG) immediately following administration of IMITREX injection. For such patients, consider periodic cardiovascular evaluation in intermittent long‑term users of IMITREX injection.

5.2 Arrhythmias

Life-threatening disturbances of cardiac rhythm, including ventricular tachycardia and ventricular fibrillation leading to death, have been reported within a few hours following the administration of 5-HT1 agonists. Discontinue IMITREX injection if these disturbances occur. IMITREX injection is contraindicated in patients with Wolff-Parkinson-White syndrome or arrhythmias associated with other cardiac accessory conduction pathway disorders.

5.3 Chest, Throat, Neck, and/or Jaw Pain/Tightness/Pressure

Sensations of tightness, pain, pressure, and heaviness in the precordium, throat, neck, and jaw commonly occur after treatment with IMITREX injection and are usually non-cardiac in origin. However, perform a cardiac evaluation if these patients are at high cardiac risk. The use of IMITREX injection is contraindicated in patients with CAD and those with Prinzmetal’s variant angina.

5.4 Cerebrovascular Events

Cerebral hemorrhage, subarachnoid hemorrhage, and stroke have occurred in patients treated with 5-HT1 agonists, and some have resulted in fatalities. In a number of cases, it appears possible that the cerebrovascular events were primary, the 5-HT1 agonist having been administered in the incorrect belief that the symptoms experienced were a consequence of migraine when they were not. Also, patients with migraine may be at increased risk of certain cerebrovascular events (e.g., stroke, hemorrhage, TIA). Discontinue IMITREX injection if a cerebrovascular event occurs.

Before treating headaches in patients not previously diagnosed with migraine or cluster headache or in patients who present with atypical symptoms, exclude other potentially serious neurological conditions. IMITREX injection is contraindicated in patients with a history of stroke or TIA.

5.5 Other Vasospasm Reactions

IMITREX injection may cause non-coronary vasospastic reactions, such as peripheral vascular ischemia, gastrointestinal vascular ischemia and infarction (presenting with abdominal pain and bloody diarrhea), splenic infarction, and Raynaud’s syndrome. In patients who experience symptoms or signs suggestive of non-coronary vasospasm reaction following the use of any 5-HT1 agonist, rule out a vasospastic reaction before receiving additional injections of IMITREX.

Reports of transient and permanent blindness and significant partial vision loss have been reported with the use of 5-HT1 agonists. Since visual disorders may be part of a migraine attack, a causal relationship between these events and the use of 5-HT1 agonists has not been clearly established.

5.6 Medication Overuse Headache

Overuse of acute migraine drugs (e.g., ergotamine, triptans, opioids, or combination of these drugs for 10 or more days per month) may lead to exacerbation of headache (medication overuse headache). Medication overuse headache may present as migraine-like daily headaches or as a marked increase in frequency of migraine attacks. Detoxification of patients, including withdrawal of the overused drugs, and treatment of withdrawal symptoms (which often includes a transient worsening of headache) may be necessary.

5.7 Serotonin Syndrome

Serotonin syndrome may occur with IMITREX injection, particularly during coadministration with selective serotonin reuptake inhibitors (SSRIs), serotonin norepinephrine reuptake inhibitors (SNRIs), tricyclic antidepressants (TCAs), and MAO inhibitors [see Drug Interactions (7.4)]. Serotonin syndrome symptoms may include mental status changes (e.g., agitation, hallucinations, coma), autonomic instability (e.g., tachycardia, labile blood pressure, hyperthermia), neuromuscular aberrations (e.g., hyperreflexia, incoordination), and/or gastrointestinal symptoms (e.g., nausea, vomiting, diarrhea). The onset of symptoms usually occurs within minutes to hours of receiving a new or a greater dose of a serotonergic medication. Discontinue IMITREX injection if serotonin syndrome is suspected.

5.8 Increase in Blood Pressure

Significant elevation in blood pressure, including hypertensive crisis with acute impairment of organ systems, has been reported on rare occasions in patients treated with 5-HT1 agonists, including patients without a history of hypertension. Monitor blood pressure in patients treated with IMITREX. IMITREX injection is contraindicated in patients with uncontrolled hypertension.

5.9 Hypersensitivity Reactions

Hypersensitivity reactions, including angioedema and anaphylaxis, have occurred in patients receiving IMITREX. Such reactions can be life-threatening or fatal. In general, anaphylactic reactions to drugs are more likely to occur in individuals with a history of sensitivity to multiple allergens. IMITREX injection is contraindicated in patients with a history of hypersensitivity reaction to IMITREX.

The needle shield of the prefilled syringe contains dry natural rubber (a latex derivative) that has the potential to cause allergic reactions in latex-sensitive individuals.

5.10 Seizures

Seizures have been reported following administration of IMITREX. Some have occurred in patients with either a history of seizures or concurrent conditions predisposing to seizures. There are also reports in patients where no such predisposing factors are apparent. IMITREX injection should be used with caution in patients with a history of epilepsy or conditions associated with a lowered seizure threshold.

6 ADVERSE REACTIONS

The following serious adverse reactions are described below and elsewhere in the labeling:

- Myocardial ischemia, myocardial infarction, and Prinzmetal’s angina [see Warnings and Precautions (5.1)]
- Arrhythmias [see Warnings and Precautions (5.2)]
- Chest, throat, neck, and/or jaw pain/tightness/pressure [see Warnings and Precautions (5.3)]
- Cerebrovascular events [see Warnings and Precautions (5.4)]
- Other vasospasm reactions [see Warnings and Precautions (5.5)]
- Medication overuse headache [see Warnings and Precautions (5.6)]
- Serotonin syndrome [see Warnings and Precautions (5.7)]
- Increase in blood pressure [see Warnings and Precautions (5.8)]
- Hypersensitivity reactions [see Contraindications (4), Warnings and Precautions (5.9)]
- Seizures [see Warnings and Precautions (5.10)]

6.1 Clinical Trials Experience

Because clinical trials are conducted under widely varying conditions, adverse reaction rates observed in the clinical trials of a drug cannot be directly compared with rates in the clinical trials of another drug and may not reflect the rates observed in practice.

Migraine Headache

Table 1 lists adverse reactions that occurred in 2 U.S. placebo‑controlled clinical trials in patients with migraines (Studies 2 and 3) following either a single 6‑mg dose of IMITREX injection or placebo. Only reactions that occurred at a frequency of 2% or more in groups treated with IMITREX injection 6 mg and that occurred at a frequency greater than the placebo group are included in Table 1.

Table 1. Adverse Reactions in Pooled Placebo-Controlled Trials in Patients with Migraine (Studies 2 and 3)
Adverse Reaction | IMITREX Injection; 6 mg Subcutaneous; (n = 547); % | Placebo; (n = 370); %
Atypical sensations | 42 | 9
Tingling | 14 | 3
Warm/hot sensation | 11 | 4
Burning sensation | 7 | <1
Feeling of heaviness | 7 | 1
Pressure sensation | 7 | 2
Feeling of tightness | 5 | <1
Numbness | 5 | 2
Feeling strange | 2 | <1
Tight feeling in head | 2 | <1
Cardiovascular
Flushing | 7 | 2
Chest discomfort | 5 | 1
Tightness in chest | 3 | <1
Pressure in chest | 2 | <1
Ear, nose, and throat
Throat discomfort | 3 | <1
Discomfort: nasal cavity/sinuses | 2 | <1
Injection site reactiona | 59 | 24
Miscellaneous
Jaw discomfort | 2 | 0
Musculoskeletal
Weakness | 5 | <1
Neck pain/stiffness | 5 | <1
Myalgia | 2 | <1
Neurological
Dizziness/vertigo | 12 | 4
Drowsiness/sedation | 3 | 2
Headache | 2 | <1
Skin
Sweating | 2 | 1

a Includes injection site pain, stinging/burning, swelling, erythema, bruising, bleeding.

The incidence of adverse reactions in controlled clinical trials was not affected by gender or age of the patients. There were insufficient data to assess the impact of race on the incidence of adverse reactions.

Cluster Headache

In the controlled clinical trials assessing the efficacy of IMITREX injection as a treatment for cluster headache (Studies 4 and 5), no new significant adverse reactions were detected that had not already been identified in trials of IMITREX in patients with migraine.

Overall, the frequency of adverse reactions reported in the trials of cluster headache was generally lower than in the migraine trials. Exceptions include reports of paresthesia (5% IMITREX injection, 0% placebo), nausea and vomiting (4% IMITREX injection, 0% placebo), and bronchospasm (1% IMITREX injection, 0% placebo).

6.2 Postmarketing Experience

The following adverse reactions have been identified during postapproval use of IMITREX tablets, IMITREX nasal spray, and IMITREX injection. Because these reactions are reported voluntarily from a population of uncertain size, it is not always possible to reliably estimate their frequency or establish a causal relationship to drug exposure.

Cardiovascular

Hypotension, palpitations.

Neurological

Dystonia, tremor.

Reproductive System and Breast Disorders

Breast pain [see Use in Specific Populations (8.2)].

7 DRUG INTERACTIONS

7.1 Ergot-Containing Drugs

Ergot-containing drugs have been reported to cause prolonged vasospastic reactions. Because these effects may be additive, use of ergotamine-containing or ergot-type medications (like dihydroergotamine or methysergide) and IMITREX injection within 24 hours of each other is contraindicated.

7.2 Monoamine Oxidase-A Inhibitors

MAO-A inhibitors increase systemic exposure by 2-fold. Therefore, the use of IMITREX injection in patients receiving MAO-A inhibitors is contraindicated [see Clinical Pharmacology (12.3)].

7.3 Other 5-HT1 Agonists

Because their vasospastic effects may be additive, coadministration of IMITREX injection and other 5-HT1 agonists (e.g., triptans) within 24 hours of each other is contraindicated.

7.4 Selective Serotonin Reuptake Inhibitors/Serotonin Norepinephrine Reuptake Inhibitors and Serotonin Syndrome

Cases of serotonin syndrome have been reported during coadministration of triptans and SSRIs, SNRIs, TCAs, and MAO inhibitors [see Warnings and Precautions (5.7)].

8 USE IN SPECIFIC POPULATIONS

8.1 Pregnancy

Risk Summary

Data from a prospective pregnancy exposure registry and epidemiological studies of pregnant women have not detected an increased frequency of birth defects or a consistent pattern of birth defects among women exposed to sumatriptan compared with the general population (see Data). In developmental toxicity studies in rats and rabbits, oral administration of sumatriptan to pregnant animals was associated with embryolethality, fetal abnormalities, and pup mortality. When administered by the intravenous route to pregnant rabbits, sumatriptan was embryolethal (see Data).

In the U.S. general population, the estimated background risk of major birth defects and of miscarriage in clinically recognized pregnancies is 2% to 4% and 15% to 20%, respectively. The reported rate of major birth defects among deliveries to women with migraine ranged from 2.2% to 2.9% and the reported rate of miscarriage was 17%, which were similar to rates reported in women without migraine.

Clinical Considerations

Disease-Associated Maternal and/or Embryo/Fetal Risk: Several studies have suggested that women with migraine may be at increased risk of preeclampsia during pregnancy.

Data

Human Data: The Sumatriptan/Naratriptan/TREXIMET (sumatriptan and naproxen sodium) Pregnancy Registry, a population-based international prospective study, collected data for sumatriptan from January 1996 to September 2012. The Registry documented outcomes of 626 infants and fetuses exposed to sumatriptan during pregnancy (528 with earliest exposure during the first trimester, 78 during the second trimester, 16 during the third trimester, and 4 unknown). The occurrence of major birth defects (excluding fetal deaths and induced abortions without reported defects and all spontaneous pregnancy losses) during first-trimester exposure to sumatriptan was 4.2% (20/478 [95% CI: 2.6% to 6.5%]) and during any trimester of exposure was 4.2% (24/576 [95% CI: 2.7% to 6.2%]). The sample size in this study had 80% power to detect at least a 1.73- to 1.91-fold increase in the rate of major malformations. The number of exposed pregnancy outcomes accumulated during the registry was insufficient to support definitive conclusions about overall malformation risk or for making comparisons of the frequencies of specific birth defects. Of the 20 infants with reported birth defects after exposure to sumatriptan in the first trimester, 4 infants had ventricular septal defects, including one infant who was exposed to both sumatriptan and naratriptan, and 3 infants had pyloric stenosis. No other birth defect was reported for more than 2 infants in this group.

In a study using data from the Swedish Medical Birth Register, live births to women who reported using triptans or ergots during pregnancy were compared with those of women who did not. Of the 2,257 births with first-trimester exposure to sumatriptan, 107 infants were born with malformations (relative risk 0.99 [95% CI: 0.91 to 1.21]). A study using linked data from the Medical Birth Registry of Norway to the Norwegian Prescription Database compared pregnancy outcomes in women who redeemed prescriptions for triptans during pregnancy, as well as a migraine disease comparison group who redeemed prescriptions for sumatriptan before pregnancy only, compared with a population control group. Of the 415 women who redeemed prescriptions for sumatriptan during the first trimester, 15 had infants with major congenital malformations (OR 1.16 [95% CI: 0.69 to 1.94]) while for the 364 women who redeemed prescriptions for sumatriptan before, but not during, pregnancy, 20 had infants with major congenital malformations (OR 1.83 [95% CI: 1.17 to 2.88]), each compared with the population comparison group. Additional smaller observational studies evaluating use of sumatriptan during pregnancy have not suggested an increased risk of teratogenicity.

Animal Data: Oral administration of sumatriptan to pregnant rats during the period of organogenesis resulted in an increased incidence of fetal blood vessel (cervicothoracic and umbilical) abnormalities. The highest no-effect dose for embryofetal developmental toxicity in rats was 60 mg/kg/day. Oral administration of sumatriptan to pregnant rabbits during the period of organogenesis resulted in increased incidences of embryolethality and fetal cervicothoracic vascular and skeletal abnormalities. Intravenous administration of sumatriptan to pregnant rabbits during the period of organogenesis resulted in an increased incidence of embryolethality. The highest oral and intravenous no-effect doses for developmental toxicity in rabbits were 15 and 0.75 mg/kg/day, respectively.

Oral administration of sumatriptan to rats prior to and throughout gestation resulted in embryofetal toxicity (decreased body weight, decreased ossification, increased incidence of skeletal abnormalities). The highest no-effect dose was 50 mg/kg/day. In offspring of pregnant rats treated orally with sumatriptan during organogenesis, there was a decrease in pup survival. The highest no-effect dose for this effect was 60 mg/kg/day. Oral treatment of pregnant rats with sumatriptan during the latter part of gestation and throughout lactation resulted in a decrease in pup survival. The highest no-effect dose for this finding was 100 mg/kg/day.

8.2 Lactation

Risk Summary

Sumatriptan is excreted in human milk following subcutaneous administration. There are no data on the effects of sumatriptan on the breastfed infant or the effects of sumatriptan on milk production. Use of sumatriptan may be associated with transient breast pain [see Adverse Reactions (6.2)].

The developmental and health benefits of breastfeeding should be considered along with the mother’s clinical need for IMITREX injection and any potential adverse effects on the breastfed infant from sumatriptan or from the underlying maternal condition.

Clinical Considerations

Infant exposure to sumatriptan can be minimized by avoiding breastfeeding for 12 hours after treatment with IMITREX injection.

8.4 Pediatric Use

Safety and effectiveness in pediatric patients have not been established. IMITREX injection is not recommended for use in patients younger than 18 years of age.

Two controlled clinical trials evaluated IMITREX nasal spray (5 to 20 mg) in 1,248 pediatric migraineurs aged 12 to 17 years who treated a single attack. The trials did not establish the efficacy of IMITREX nasal spray compared with placebo in the treatment of migraine in pediatric patients. Adverse reactions observed in these clinical trials were similar in nature to those reported in clinical trials in adults.

Five controlled clinical trials (2 single-attack trials, 3 multiple-attack trials) evaluating oral IMITREX (25 to 100 mg) in pediatric patients aged 12 to 17 years enrolled a total of 701 pediatric migraineurs. These trials did not establish the efficacy of oral IMITREX compared with placebo in the treatment of migraine in pediatric patients. Adverse reactions observed in these clinical trials were similar in nature to those reported in clinical trials in adults. The frequency of all adverse reactions in these patients appeared to be both dose- and age‑dependent, with younger patients reporting reactions more commonly than older pediatric patients.

Postmarketing experience documents that serious adverse reactions have occurred in the pediatric population after use of subcutaneous, oral, and/or intranasal IMITREX. These reports include reactions similar in nature to those reported rarely in adults, including stroke, visual loss, and death. A myocardial infarction has been reported in a 14-year-old male following the use of oral IMITREX; clinical signs occurred within 1 day of drug administration. Clinical data to determine the frequency of serious adverse reactions in pediatric patients who might receive subcutaneous, oral, or intranasal IMITREX are not presently available.

8.5 Geriatric Use

Clinical trials of IMITREX injection did not include sufficient numbers of patients aged 65 years and older to determine whether they respond differently from younger patients. Other reported clinical experience has not identified differences in responses between the elderly and younger patients. In general, dose selection for an elderly patient should be cautious, usually starting at the low end of the dosing range, reflecting the greater frequency of decreased hepatic, renal, or cardiac function and of concomitant disease or other drug therapy.

A cardiovascular evaluation is recommended for geriatric patients who have other cardiovascular risk factors (e.g., diabetes, hypertension, smoking, obesity, strong family history of CAD) prior to receiving IMITREX injection [see Warnings and Precautions (5.1)].

10 OVERDOSAGE

Coronary vasospasm was observed after intravenous administration of IMITREX injection [see Contraindications (4)]. Overdoses would be expected from animal data (dogs at 0.1 g/kg, rats at 2 g/kg) to possibly cause convulsions, tremor, inactivity, erythema of the extremities, reduced respiratory rate, cyanosis, ataxia, mydriasis, injection site reactions (desquamation, hair loss, and scab formation), and paralysis.

The elimination half-life of sumatriptan is about 2 hours [see Clinical Pharmacology (12.3)]; therefore, monitoring of patients after overdose with IMITREX injection should continue for at least 10 hours or while symptoms or signs persist.

It is unknown what effect hemodialysis or peritoneal dialysis has on the serum concentrations of sumatriptan.

11 DESCRIPTION

IMITREX injection contains sumatriptan succinate, a selective 5-HT1B/1D receptor agonist. Sumatriptan succinate is chemically designated as 3-[2-(dimethylamino)ethyl]-N-methyl-indole-5-methanesulfonamide succinate (1:1), and it has the following structure:

The empirical formula is C14H21N3O2S•C4H6O4, representing a molecular weight of 413.5. Sumatriptan succinate is a white to off-white powder that is readily soluble in water and in saline.

IMITREX injection is a clear, colorless to pale yellow, sterile, nonpyrogenic solution for subcutaneous injection. Each 0.5 mL of IMITREX injection 8-mg/mL solution contains 5.6 mg of sumatriptan succinate equivalent to 4 mg of sumatriptan and 3.8 mg of sodium chloride, USP in Water for Injection, USP. Each 0.5 mL of IMITREX injection 12-mg/mL solution contains 8.4 mg of sumatriptan succinate equivalent to 6 mg of sumatriptan and 3.5 mg of sodium chloride, USP in Water for Injection, USP. The pH range of both solutions is approximately 4.2 to 5.3. The osmolality of both injections is 291 mOsmol.

12 CLINICAL PHARMACOLOGY

12.1 Mechanism of Action

Sumatriptan binds with high affinity to human cloned 5-HT1B/1D receptors. Sumatriptan presumably exerts its therapeutic effects in the treatment of migraine and cluster headaches through agonist effects at the 5-HT1B/1D receptors on intracranial blood vessels and sensory nerves of the trigeminal system, which result in cranial vessel constriction and inhibition of pro‑inflammatory neuropeptide release.

12.2 Pharmacodynamics

Blood Pressure

Significant elevation in blood pressure, including hypertensive crisis, has been reported in patients with and without a history of hypertension [see Warnings and Precautions (5.8)].

Peripheral (Small) Arteries

In healthy volunteers (N = 18), a trial evaluating the effects of sumatriptan on peripheral (small vessel) arterial reactivity failed to detect a clinically significant increase in peripheral resistance.

Heart Rate

Transient increases in blood pressure observed in some patients in clinical trials carried out during sumatriptan’s development as a treatment for migraine were not accompanied by any clinically significant changes in heart rate.

12.3 Pharmacokinetics

Absorption

The bioavailability of sumatriptan via subcutaneous site injection to 18 healthy male subjects was 97% ± 16% of that obtained following intravenous injection.

After a single 6-mg subcutaneous manual injection into the deltoid area of the arm in 18 healthy males (age: 24 ± 6 years, weight: 70 kg), the maximum serum concentration (Cmax) of sumatriptan was (mean ± standard deviation) 74 ± 15 ng/mL and the time to peak concentration (Tmax) was 12 minutes after injection (range: 5 to 20 minutes). In this trial, the same dose injected subcutaneously in the thigh gave a Cmax of 61 ± 15 ng/mL by manual injection versus 52 ± 15 ng/mL by autoinjector techniques. The Tmax or amount absorbed was not significantly altered by either the site or technique of injection.

Distribution

Protein binding, determined by equilibrium dialysis over the concentration range of 10 to 1,000 ng/mL is low, approximately 14% to 21%. The effect of sumatriptan on the protein binding of other drugs has not been evaluated.

Following a 6-mg subcutaneous injection into the deltoid area of the arm in 9 males (mean age: 33 years, mean weight: 77 kg) the volume of distribution central compartment of sumatriptan was 50 ± 8 liters and the distribution half‑life was 15 ± 2 minutes.

Metabolism

In vitro studies with human microsomes suggest that sumatriptan is metabolized by MAO, predominantly the A isoenzyme. Most of a radiolabeled dose of sumatriptan excreted in the urine is the major metabolite indole acetic acid (IAA) or the IAA glucuronide, both of which are inactive.

Elimination

After a single 6-mg subcutaneous dose, 22% ± 4% was excreted in the urine as unchanged sumatriptan and 38% ± 7% as the IAA metabolite.

Following a 6-mg subcutaneous injection into the deltoid area of the arm, the systemic clearance of sumatriptan was 1,194 ± 149 mL/min and the terminal half-life was 115 ± 19 minutes.

Specific Populations

Age: The pharmacokinetics of sumatriptan in the elderly (mean age: 72 years, 2 males and 4 females) and in subjects with migraine (mean age: 38 years, 25 males and 155 females) were similar to that in healthy male subjects (mean age: 30 years).

Patients with Hepatic Impairment: The effect of mild to moderate hepatic disease on the pharmacokinetics of subcutaneously administered sumatriptan has been evaluated. There were no significant differences in the pharmacokinetics of subcutaneously administered sumatriptan in moderately hepatically impaired subjects compared with healthy controls. The pharmacokinetics of subcutaneously administered sumatriptan in patients with severe hepatic impairment has not been studied. The use of IMITREX injection in this population is contraindicated [see Contraindications (4)].

Racial Groups: The systemic clearance and Cmax of subcutaneous sumatriptan were similar in black (n = 34) and Caucasian (n = 38) healthy male subjects.

Drug Interaction Studies

Monoamine Oxidase-A Inhibitors: In a trial of 14 healthy females, pretreatment with an MAO-A inhibitor decreased the clearance of subcutaneous sumatriptan, resulting in a 2-fold increase in the area under the sumatriptan plasma concentration-time curve (AUC), corresponding to a 40% increase in elimination half-life.

13 NONCLINICAL TOXICOLOGY

13.1 Carcinogenesis, Mutagenesis, Impairment of Fertility

Carcinogenesis

In carcinogenicity studies in mouse and rat, sumatriptan was administered orally for 78 weeks and 104 weeks, respectively, at doses up to 160 mg/kg/day (the high dose in rat was reduced from 360 mg/kg/day during Week 21). The highest dose to mice and rats was approximately 130 and 260 times the single maximum recommended human dose (MRHD) of 6 mg administered subcutaneously on a mg/m^2 basis. There was no evidence in either species of an increase in tumors related to sumatriptan administration.

Mutagenesis

Sumatriptan was negative in in vitro (bacterial reverse mutation [Ames], gene cell mutation in Chinese hamster V79/HGPRT, chromosomal aberration in human lymphocytes) and in vivo (rat micronucleus) assays.

Impairment of Fertility

When sumatriptan (5, 50, 500 mg/kg/day) was administered orally to male and female rats prior to and throughout the mating period, there was a treatment-related decrease in fertility secondary to a decrease in mating in animals treated with doses greater than 5 mg/kg/day. It is not clear whether this finding was due to an effect on males or females or both.

When sumatriptan was administered by subcutaneous injection to male and female rats prior to and throughout the mating period, there was no evidence of impaired fertility at doses up to 60 mg/kg/day.

13.2 Animal Toxicology and/or Pharmacology

Corneal Opacities

Dogs receiving oral sumatriptan developed corneal opacities and defects in the corneal epithelium. Corneal opacities were seen at the lowest dose tested, 2 mg/kg/day, and were present after 1 month of treatment. Defects in the corneal epithelium were noted in a 60-week study. Earlier examinations for these toxicities were not conducted and no-effect doses were not established; however, the relative plasma exposure at the lowest dose tested was approximately 3 times the human exposure after a 6-mg subcutaneous dose.

14 CLINICAL STUDIES

14.1 Migraine

In controlled clinical trials enrolling more than 1,000 patients during migraine attacks who were experiencing moderate or severe pain and 1 or more of the symptoms enumerated in Table 3, onset of relief began as early as 10 minutes following a 6-mg IMITREX injection. Lower doses of IMITREX injection may also prove effective, although the proportion of patients obtaining adequate relief was decreased and the latency to that relief is greater with lower doses.

In Study 1, 6 different doses of IMITREX injection (n = 30 each group) were compared with placebo (n = 62) in a single-attack, parallel-group design; the dose-response relationship was found to be as shown in Table 2.

Table 2. Proportion of Patients with Migraine Relief and Incidence of Adverse Reactions by Time and by Dose of IMITREX in Study 1
Dose of IMITREX Injection | Percent Patients with Reliefa |  |  |  | Adverse Reactions Incidence (%)
Dose of IMITREX Injection | at 10 Minutes | at 30 Minutes | at 1 Hour | at 2 Hours | Adverse Reactions Incidence (%)
Placebo | 5 | 15 | 24 | 21 | 55
1 mg | 10 | 40 | 43 | 40 | 63
2 mg | 7 | 23 | 57 | 43 | 63
3 mg | 17 | 47 | 57 | 60 | 77
4 mg | 13 | 37 | 50 | 57 | 80
6 mg | 10 | 63 | 73 | 70 | 83
8 mg | 23 | 57 | 80 | 83 | 93

a Relief is defined as the reduction of moderate or severe pain to no or mild pain after dosing without use of rescue medication.

In 2 randomized, placebo-controlled clinical trials of IMITREX injection 6 mg in 1,104 patients with moderate or severe migraine pain (Studies 2 and 3), the onset of relief was less than 10 minutes. Headache relief, as defined by a reduction in pain from severe or moderately severe to mild or no headache, was achieved in 70% of the patients within 1 hour of a single 6-mg subcutaneous dose of IMITREX injection. Approximately 82% and 65% of patients treated with IMITREX 6 mg had headache relief and were pain free within 2 hours, respectively.

Table 3 shows the 1- and 2-hour efficacy results for IMITREX injection 6 mg in Studies 2 and 3.

Table 3. Proportion of Patients with Pain Relief and Relief of Migraine Symptoms after 1 and 2 Hours of Treatment in Studies 2 and 3
1-Hour Data | Study 2 |  | Study 3
1-Hour Data | Placebo; (n = 190) | IMITREX; 6 mg; (n = 384) | Placebo; (n = 180) | IMITREX 6 mg; (n = 350)
Patients with pain relief (Grade 0/1) | 18% | 70%a | 26% | 70%a
Patients with no pain | 5% | 48%a | 13% | 49%a
Patients without nausea | 48% | 73%a | 50% | 73%a
Patients without photophobia | 23% | 56%a | 25% | 58%a
Patients with little or no clinical disabilityb | 34% | 76%a | 34% | 76%a
2-Hour Data | Study 2 |  | Study 3
2-Hour Data | Placeboc | IMITREX; 6 mgd | Placeboc | IMITREX; 6 mgd
Patients with pain relief (Grade 0/1) | 31% | 81%a | 39% | 82%a
Patients with no pain | 11% | 63%a | 19% | 65%a
Patients without nausea | 56% | 82%a | 63% | 81%a
Patients without photophobia | 31% | 72%a | 35% | 71%a
Patients with little or no clinical disabilityb | 42% | 85%a | 49% | 84%a

a P<0.05 versus placebo.
b A successful outcome in terms of clinical disability was defined prospectively as ability to work mildly impaired or ability to work and function normally.
c Includes patients that may have received an additional placebo injection 1 hour after the initial injection.
d Includes patients that may have received an additional 6 mg of IMITREX injection 1 hour after the initial injection.

IMITREX injection also relieved photophobia, phonophobia (sound sensitivity), nausea, and vomiting associated with migraine attacks. Similar efficacy was seen when patients self-administered IMITREX injection using the IMITREX STATdose Pen.

The efficacy of IMITREX injection was unaffected by whether or not the migraine was associated with aura, duration of attack, gender or age of the patient, or concomitant use of common migraine prophylactic drugs (e.g., beta-blockers).

14.2 Cluster Headache

The efficacy of IMITREX injection in the acute treatment of cluster headache was demonstrated in 2 randomized, double-blind, placebo-controlled, 2-period crossover trials (Studies 4 and 5). Patients aged 21 to 65 years were enrolled and were instructed to treat a moderate to very severe headache within 10 minutes of onset. Headache relief was defined as a reduction in headache severity to mild or no pain. In both trials, the proportion of individuals gaining relief at 10 or 15 minutes was significantly greater among patients receiving 6 mg of IMITREX injection compared with those who received placebo (see Table 4).

Table 4. Proportion of Patients with Cluster Headache Relief by Time in Studies 4 and 5
 | Study 4 |  | Study 5
 | Placebo; (n = 39) | IMITREX; 6 mg; (n = 39) | Placebo; (n = 88) | IMITREX; 6 mg; (n = 92)
Patients with pain relief (no/mild)
5 Minutes post-injection | 8% | 21% | 7% | 23%a
10 Minutes post-injection | 10% | 49%a | 25% | 49%a
15 Minutes post-injection | 26% | 74%a | 35% | 75%a

a P<0.05.
n = Number of headaches treated.

An estimate of the cumulative probability of a patient with a cluster headache obtaining relief after being treated with either IMITREX injection or placebo is presented in Figure 1.

Figure 1. Time to Relief of Cluster Headache from Time of Injectiona

a The figure uses Kaplan-Meier (product limit) Survivorship Plot. Patients taking rescue medication were censored at 15 minutes.

The plot was constructed with data from patients who either experienced relief or did not require (request) rescue medication within a period of 2 hours following treatment. As a consequence, the data in the plot are derived from only a subset of the 258 headaches treated (rescue medication was required in 52 of the 127 placebo-treated headaches and 18 of the 131 headaches treated with IMITREX injection).

Other data suggest that treatment with IMITREX injection is not associated with an increase in early recurrence of headache and has little effect on the incidence of later-occurring headaches (i.e., those occurring after 2, but before 18 or 24 hours).

16 HOW SUPPLIED/STORAGE AND HANDLING

IMITREX injection contains sumatriptan (base) as the succinate salt and is supplied as a clear, colorless to pale yellow, sterile, nonpyrogenic solution as follows:

Prefilled Syringe and/or Autoinjector Pen:

The needle shield of the prefilled syringe contains dry natural rubber (a latex derivative) that has the potential to cause allergic reactions in latex-sensitive individuals.

Each pack contains a Patient Information and Instructions for Use leaflet.

- IMITREX STATdose System, 4 mg, containing 1 IMITREX STATdose Pen, 2 prefilled single-dose syringe cartridges, and 1 carrying case (NDC 0173-0739-00).
- IMITREX STATdose System, 6 mg, containing 1 IMITREX STATdose Pen, 2 prefilled single-dose syringe cartridges, and 1 carrying case (NDC 0173-0479-00).
- Two 4-mg single-dose prefilled syringe cartridges for use with IMITREX STATdose System (NDC 0173-0739-02).
- Two 6-mg single-dose prefilled syringe cartridges for use with IMITREX STATdose System (NDC 0173-0478-00).

Store between 2° and 30°C (36° and 86°F). Protect from light.

17 PATIENT COUNSELING INFORMATION

Advise the patient to read the FDA-approved patient labeling (Patient Information and Instructions for Use).

Risk of Myocardial Ischemia and/or Infarction, Prinzmetal’s Angina, Other Vasospasm-Related Events, Arrhythmias, and Cerebrovascular Events

Inform patients that IMITREX injection may cause serious cardiovascular side effects such as myocardial infarction or stroke. Although serious cardiovascular events can occur without warning symptoms, patients should be alert for the signs and symptoms of chest pain, shortness of breath, irregular heartbeat, significant rise in blood pressure, weakness, and slurring of speech, and should ask for medical advice if any indicative sign or symptoms are observed. Apprise patients of the importance of this follow-up [see Warnings and Precautions (5.1, 5.2, 5.4, 5.5, 5.8)].

Hypersensitivity Reactions

Inform patients that anaphylactic reactions have occurred in patients receiving IMITREX injection. Such reactions can be life-threatening or fatal. In general, anaphylactic reactions to drugs are more likely to occur in individuals with a history of sensitivity to multiple allergens [see Contraindications (4), Warnings and Precautions (5.9)]. Inform latex-sensitive patients that the needle shield of the IMITREX prefilled syringe contains dry natural rubber (a derivative of latex) that may cause allergic reactions in individuals sensitive to latex.

Concomitant Use with Other Triptans or Ergot Medications

Inform patients that use of IMITREX injection within 24 hours of another triptan or an ergot-type medication (including dihydroergotamine or methysergide) is contraindicated [see Contraindications (4), Drug Interactions (7.1, 7.3)].

Serotonin Syndrome

Caution patients about the risk of serotonin syndrome with the use of IMITREX injection or other triptans, particularly during combined use with SSRIs, SNRIs, TCAs, and MAO inhibitors [see Warnings and Precautions (5.7), Drug Interactions (7.4)].

Medication Overuse Headache

Inform patients that use of acute migraine drugs for 10 or more days per month may lead to an exacerbation of headache and encourage patients to record headache frequency and drug use (e.g., by keeping a headache diary) [see Warnings and Precautions (5.6)].

Pregnancy

Advise patients to notify their healthcare provider if they become pregnant during treatment or plan to become pregnant [see Use in Specific Populations (8.1)].

Lactation

Advise breastfeeding women that they may develop transient breast pain when taking IMITREX. Advise breastfeeding women that avoiding breastfeeding for 12 hours after treatment with IMITREX can minimize their infant’s exposure to sumatriptan [see Use in Specific Populations (8.2)].

Ability to Perform Complex Tasks

Treatment with IMITREX injection may cause somnolence and dizziness; instruct patients to evaluate their ability to perform complex tasks after administration of IMITREX injection.

How to Use IMITREX injection

Instruct patients to read the Instructions for Use before starting therapy. Provide patients instruction on the proper use of IMITREX injection if they are able to self-administer IMITREX injection in medically unsupervised situations. Instruct patients on storage and disposal of the pen [see How Supplied/Storage and Handling (16)].

Inform patients that the needle in the IMITREX STATdose Pen penetrates approximately 1/4 of an inch (5 to 6 mm). Inform patients that the injection is intended to be given subcutaneously and intramuscular or intravascular delivery should be avoided. Instruct patients to use injection sites with an adequate skin and subcutaneous thickness to accommodate the length of the needle.

IMITREX, IMITREX STATdose System and IMITREX STATdose Pen are trademarks owned by or licensed to the GSK group of companies. The other brand listed is a trademark owned by or licensed to its owner and is not owned by or licensed to the GSK group of companies. The maker of this brand is not affiliated with and does not endorse the GSK group of companies or its products.

GlaxoSmithKline
Durham, NC 27701

©2025 GSK group of companies or its licensor.

IMJ:13PI

PATIENT INFORMATION

PATIENT INFORMATION

IMITREX (IM-i-trex)

(sumatriptan)

injection

What is the most important information I should know about IMITREX?

IMITREX can cause serious side effects, including:

Heart attack and other heart problems. Heart problems may lead to death.

Stop taking IMITREX and get emergency medical help right away if you have any of the following symptoms of a heart attack:

- discomfort in the center of your chest that lasts for more than a few minutes, or that goes away and comes back
- severe tightness, pain, pressure, or heaviness in your chest, throat, neck, or jaw
- pain or discomfort in your arms, back, neck, jaw, or stomach
- shortness of breath with or without chest discomfort
- breaking out in a cold sweat
- nausea or vomiting
- feeling lightheaded

IMITREX is not for people with risk factors for heart disease unless a heart exam is done and shows no problem. You have a higher risk for heart disease if you:

- have high blood pressure
- have high cholesterol levels
- smoke
- are overweight
- have diabetes
- have a family history of heart disease

What is IMITREX?

IMITREX injection is a prescription medicine used to treat acute migraine headaches with or without aura and acute cluster headaches in adults who have been diagnosed with migraine or cluster headaches.

IMITREX is not used to treat other types of headaches such as hemiplegic (that make you unable to move on one side of your body) or basilar (rare form of migraine with aura) migraines.

IMITREX is not used to prevent or decrease the number of migraine or cluster headaches you have.

It is not known if IMITREX is safe and effective in children under 18 years of age.

Do not take IMITREX if you have:

- heart problems or a history of heart problems.
- narrowing of blood vessels to your legs, arms, stomach, or kidneys (peripheral vascular disease).
- uncontrolled high blood pressure.
- severe liver problems.
- hemiplegic migraines or basilar migraines. If you are not sure if you have these types of migraines, ask your healthcare provider.
- had a stroke, transient ischemic attacks (TIAs), or problems with your blood circulation.
- taken any of the following medicines in the last 24 hours:

- almotriptan (AXERT)
- frovatriptan (FROVA)
- rizatriptan (MAXALT, MAXALT-MLT)
- ergotamines (CAFERGOT, ERGOMAR, MIGERGOT)

- eletriptan (RELPAX)
- naratriptan (AMERGE)
- sumatriptan and naproxen (TREXIMET)
- dihydroergotamine (D.H.E. 45, MIGRANAL)

Ask your healthcare provider if you are not sure if your medicine is listed above.
2. an allergy to sumatriptan or any of the ingredients in IMITREX. See the end of this leaflet for a complete list of ingredients in IMITREX.

Before taking IMITREX, tell your healthcare provider about all of your medical conditions, including if you:

- have high blood pressure
- have high cholesterol
- have diabetes
- smoke
- are overweight
- have heart problems or family history of heart problems or stroke
- have kidney problems
- have liver problems
- are allergic to latex
- have had epilepsy or seizures
- are not using effective birth control
- are pregnant or plan to become pregnant. It is not known if IMITREX can harm your unborn baby.
- are breastfeeding or plan to breastfeed. IMITREX passes into your breast milk. It is not known if this can harm your baby. Talk with your healthcare provider about the best way to feed your baby if you take IMITREX.

Tell your healthcare provider about all the medicines you take, including prescription and over-the-counter medicines, vitamins, and herbal supplements.

IMITREX and certain other medicines can affect each other, causing serious side effects.

Especially tell your healthcare provider if you take antidepressant medicines called:

- selective serotonin reuptake inhibitors (SSRIs)
- serotonin norepinephrine reuptake inhibitors (SNRIs)
- tricyclic antidepressants (TCAs)
- monoamine oxidase inhibitors (MAOIs)

Ask your healthcare provider or pharmacist for a list of these medicines if you are not sure.

Know the medicines you take. Keep a list of them to show your healthcare provider or pharmacist when you get a new medicine.

How should I take IMITREX?

- Certain people should take their first dose of IMITREX in their healthcare provider’s office or in another medical setting. Ask your healthcare provider if you should take your first dose in a medical setting.
- Use IMITREX exactly as your healthcare provider tells you to use it.
- Your healthcare provider may change your dose. Do not change your dose without first talking with your healthcare provider.
- For adults, the usual dose is a single injection given just below the skin.
- You should give an injection as soon as the symptoms of your headache start, but it may be given at any time during a migraine or cluster headache attack.
- If you did not get any relief after the first injection, do not give a second injection without first talking with your healthcare provider.
- If your headache comes back or you only get some relief after your first injection, you can take a second injection 1 hour after the first injection, but not sooner.
- Do not take more than 12 mg in a 24‑hour period.
- If you use too much IMITREX, call your healthcare provider or go to the nearest hospital emergency room right away.
- You should write down when you have headaches and when you take IMITREX so you can talk with your healthcare provider about how IMITREX is working for you.

What should I avoid while taking IMITREX?

IMITREX can cause dizziness, weakness, or drowsiness. If you have these symptoms, do not drive a car, use machinery, or do anything where you need to be alert.

What are the possible side effects of IMITREX?

IMITREX may cause serious side effects. See “What is the most important information I should know about IMITREX?”

These serious side effects include:

- changes in color or sensation in your fingers and toes (Raynaud’s syndrome)
- stomach and intestinal problems (gastrointestinal and colonic ischemic events). Symptoms of gastrointestinal and colonic ischemic events include:

- sudden or severe stomach pain
- stomach pain after meals
- weight loss
- fever

- nausea or vomiting
- constipation or diarrhea
- bloody diarrhea

- problems with blood circulation to your legs and feet (peripheral vascular ischemia). Symptoms of peripheral vascular ischemia include:
  - cramping and pain in your legs or hips
  - feeling of heaviness or tightness in your leg muscles
  - burning or aching pain in your feet or toes while resting
  - numbness, tingling, or weakness in your legs
  - cold feeling or color changes in 1 or both legs or feet
- medication overuse headaches. Some people who use too many IMITREX injections may have worse headaches (medication overuse headache). If your headaches get worse, your healthcare provider may decide to stop your treatment with IMITREX.
- serotonin syndrome. Serotonin syndrome is a rare but serious problem that can happen in people using IMITREX, especially if IMITREX is used with anti‑depressant medicines called SSRIs or SNRIs.
Call your healthcare provider right away if you have any of the following symptoms of serotonin syndrome:
  1. mental changes such as seeing things that are not there (hallucinations), agitation, or coma
  2. fast heartbeat
  3. changes in blood pressure
  4. high body temperature
  5. tight muscles
  6. trouble walking
- hives (itchy bumps); swelling of your tongue, mouth or throat.
- seizures. Seizures have happened in people taking IMITREX who have never had seizures before. Talk with your healthcare provider about your chance of having seizures while you take IMITREX.

The most common side effects of IMITREX Injection include:

- pain or redness at your injection site
- tingling or numbness in your fingers or toes
- dizziness
- warm, hot, burning feeling to your face (flushing)
- discomfort or stiffness in your neck
- feeling weak, drowsy, or tired

Tell your healthcare provider if you have any side effect that bothers you or that does not go away.

These are not all the possible side effects of IMITREX. Call your doctor for medical advice about side effects. You may report side effects to FDA at 1-800-FDA-1088.

How should I store IMITREX injection?

- Store IMITREX between 36°F to 86°F (2°C to 30°C).
- Store your medicine away from light.
- Keep your medicine in the packaging or carrying case provided with it.

Keep IMITREX and all medicines out of the reach of children.

General information about the safe and effective use of IMITREX

Medicines are sometimes prescribed for purposes other than those listed in Patient Information leaflets. Do not use IMITREX for a condition for which it was not prescribed. Do not give IMITREX to other people, even if they have the same symptoms you have. It may harm them.

This Patient Information leaflet summarizes the most important information about IMITREX. If you would like more information, talk with your healthcare provider. You can ask your healthcare provider or pharmacist for information about IMITREX that is written for healthcare professionals.

For more information, call 1-888-825-5249.

What are the ingredients in IMITREX injection?

Active ingredient: sumatriptan succinate

Inactive ingredients: sodium chloride, water for injection

IMITREX and AMERGE are trademarks owned by or licensed to the GSK group of companies. The other brands listed are trademarks owned by or licensed to their respective owners and are not owned by or licensed to the GSK group of companies. The makers of these brands are not affiliated with and do not endorse the GSK group of companies or its products.

GlaxoSmithKline

Durham, NC 27701

©2023 GSK group of companies or its licensor.

IMJ:9PPI

This Patient Information has been approved by the U.S. Food and Drug Administration. Revised February 2023

Instructions for Use

IMITREX (IM-i-trex) STATdose System

(sumatriptan)

Injection

Read this Instructions for Use before you start to use the IMITREX STATdose System. There may be new information. This information does not take the place of talking with your healthcare provider about your medical condition or treatment. You and your healthcare provider should talk about IMITREX Injection when you start taking it and at regular checkups.

Keep the IMITREX STATdose System out of the reach of children.

Before you use the IMITREX STATdose System

When you first open the IMITREX STATdose System box, the Cartridge Pack and the IMITREX STATdose Pen are already in the Carrying Case for your convenience.

The grey and blue Carrying Case is used for storing the unloaded Pen and the Cartridge Pack when they are not being used.

- The Cartridge Pack holds 2 individually sealed Syringe Cartridges. Each Syringe Cartridge holds 1 dose of IMITREX (sumatriptan) Injection.
- The Cartridge Pack for the 4-mg strength of this medicine is yellow.
- The Cartridge Pack for the 6-mg strength is blue (as shown).
- Refill Cartridge Packs are available.

Important Things to Know About Your IMITREX STATdose System

- The needle shield of the prefilled syringe contains dry natural rubber, which is made from latex. This is a part you cannot usually see, but it could still cause an allergic reaction. Tell your healthcare provider if you are allergic to latex.
- Before you use IMITREX STATdose System your healthcare provider should show you or your caregiver how to give an injection the right way.
- The Pen is used to automatically inject 1 dose of medicine from a Syringe Cartridge.
- Before you load a Syringe Cartridge, always check to make sure that the white Priming Rod is not sticking out from the end of the Pen (as shown below in Figure B). If it is sticking out, you will lose that dose.
- Do not touch the Blue Button until you have pressed the Pen firmly against your skin to give a dose.
- The Pen will only work when the Safety Catch is released. To release the Safety Catch, you must press the Pen firmly against your skin until the grey part of the barrel slides against the blue part and it cannot be pressed any further. The grey part of the barrel must stay in contact with the blue part while you inject your medicine.
- When you inject the dose, make sure the Pen stays in contact with your skin during the injection. It is important to hold the Pen against the skin for at least 5 seconds.
- After each use the Pen must be put back into the Carrying Case to reset the white Priming Rod before the next use.

How to load the IMITREX STATdose Pen

Do not load the Pen until you are ready to give yourself an injection.
Do not touch the Blue Button on top of the Pen (see Figure A)
while you are loading the Pen.

Figure A

1. Open the lid of the Carrying Case.
  1. Your new Carrying Case will come with 2 Syringe Cartridges already inside.
  2. The tamper-evident seals over the 2 Syringe Cartridges are labeled “A” and “B” (see Figure A).
  3. Always use the Syringe Cartridge marked “A” before the one marked “B” to help you keep track of your doses. Do not use if either seal is broken or missing when you first open the Carrying Case.
Check the expiration date on the Cartridge Pack. Do not use if expired.
2. Tear off one of the tamper-evident seals (see Figure A). Throw away the seal. Open the lid over the Syringe Cartridge.

Figure B

3. Hold the Pen by the ridges at the top. Take the Pen out of the Carrying Case (see Figure B).
Check to make sure the white Priming Rod is not sticking out from the lower end of the Pen (see Figure B). If it is sticking out, put the Pen back into the Carrying Case and press down firmly until you feel it click. Take the Pen out of the Carrying Case.

Figure C

4. Put the Pen in the open Cartridge Pack. Turn it to the right (clockwise) until it will not turn any more (about half a turn) (see Figure C).

Figure D

5. Hold the loaded Pen by the ridges and pull it straight out (see Figure D). You may need to pull hard on the Pen, but this is normal. Do not press the Blue Button yet.

The Pen is now ready to use. Do not put the loaded Pen back into the Carrying Case because that will damage the needle.

How to use the IMITREX STATdose Pen to take your medicine

Figure E

6. Choose and Prepare the Injection Site.
  1. Before injecting your medicine, choose one area with a fatty tissue layer (see Figure E or Figure F).
  2. Ask your healthcare provider if you have a question about where to inject your medicine.
  3. To prepare the area of skin where IMITREX is to be injected, wipe the injection site with an alcohol swab.
  4. Do not touch this area again before giving the injection. Be sure to change the injection site with each dose.

Figure F

7. Inject with the IMITREX STATdose Pen.
  1. Without pushing the Blue Button, press the loaded Pen firmly against the skin so that the grey part of the barrel slides against the blue part until it cannot be pressed any further. Make sure the grey part of the barrel stays in contact with the blue part that holds the Syringe Cartridge. This releases the Safety Catch that keeps the Pen from giving your injection by mistake or until you are ready (see Figure F).

Figure G

- With the Pen still pressed firmly against the skin, push the Blue Button (see Figure G).
- Hold the Pen still for at least 5 seconds against the skin. If the Pen is taken away from your skin too soon, you will not receive all the medicine or it may leak out of the Pen.

Figure H

8. Remove STATdose Pen from your skin.
2. After 5 seconds, carefully take the Pen away from your skin. The needle will be showing (see Figure H).
3. Do not touch the needle.

How to unload the IMITREX STATdose Pen after taking your medicine

Right after you complete your injection with the Pen, you need to return the used Syringe Cartridge to the Cartridge Pack.

Figure I

9. Push the Pen down into the empty side of the Cartridge Pack as far as it will go (see Figure I).

Figure J

10. Turn the Pen to the left (counterclockwise) about half a turn until it is released from the Syringe Cartridge (see Figure J).

Figure K

11. Pull the empty Pen out of the Cartridge Pack.
  1. Because the Pen has now been used, the white Priming Rod will stick out from the lower end of the Pen (see Figure K).
12. Close the Cartridge Pack lid over the used Syringe Cartridge.
  1. When the used Syringe Cartridges are inserted correctly, the Cartridge Pack is a disposable, protective case to help you avoid needle sticks.
13. Put the Pen back into the Carrying Case and press it down firmly until you feel it click.
  1. This step is important to reset the Pen so that the white Priming Rod does not stick out and to get the Pen ready for the next use.
14. Close the Carrying Case lid.
  1. If the lid will not close, push the Pen down until you feel it click. Then close the lid.

How to take out a used Cartridge Pack

After both Syringe Cartridges have been used, take the Cartridge Pack out of the Carrying Case. Do not reuse or recycle a Syringe Cartridge.

Figure L

15. Open the Carrying Case lid.
16. Hold the Carrying Case with one hand and press the 2 buttons on either side of the Carrying Case (see Figure L).

Figure M

17. Gently pull out the Cartridge Pack with the other hand (see Figure M).
18. Throw away the Cartridge Pack or dispose of it as instructed by your healthcare provider. See “How to Dispose of your used Syringe Cartridge Pack” below.
There may be special state and local laws for disposing of used needles and syringes.

How to insert a new Cartridge Pack

Figure N

19. Take the new Cartridge Pack out of its box. Do not take off the tamper‑evident seals (see Figure N).

Figure O

20. Put the Cartridge Pack in the Carrying Case. Slide it down smoothly (see Figure O).

Figure P

21. The Cartridge Pack will click into place when the 2 buttons show through the holes in the Carrying Case (see Figure P). Close the lid.

How to dispose of your used Syringe Cartridge Pack

Put your used syringe cartridge pack in an FDA-cleared sharps disposal container right away after use (see Figure Q). Do not throw away (dispose of) loose needles and syringes in your household trash.

Figure Q

- If you do not have an FDA-cleared sharps disposal container, you may use a household container that is:
  - made of a heavy-duty plastic,
  - can be closed with a tight-fitting, puncture-resistant lid, without sharps being able to come out, upright and stable during use,
  - leak-resistant, and
  - properly labeled to warn of hazardous waste inside the container.
- When your sharps disposal container is almost full, you will need to follow your community guidelines for the right way to dispose of your sharps disposal container. There may be state or local laws about how you should throw away used needles and cartridges. For more information about safe sharps disposal, and for specific information about sharps disposal in the state that you live in, go to the FDA’s website at: http://www.fda.gov/safesharpsdisposal.
- Do not dispose of your used sharps disposal container in your household trash unless your community guidelines permit this. Do not recycle your used sharps disposal container.

This Patient Information and Instructions for Use has been approved by the U.S. Food and Drug Administration.

Trademarks are owned by or licensed to the GSK group of companies.

GlaxoSmithKline

Durham, NC 27701

©2023 GSK group of companies or its licensor.

February 2023

IMJ:10PIL

PACKAGE LABEL

PRINCIPAL DISPLAY PANEL

NDC 0173-0739-02

IMITREX

(SUMATRIPTAN)

INJECTION

4 mg

0.5 mL

For subcutaneous injection only.

2 Single-Dose Syringe Cartridges

Rx only

62000000090054 Rev. 10/23

PACKAGE LABEL

PRINCIPAL DISPLAY PANEL

NDC 0173-0478-00

IMITREX

(SUMATRIPTAN)

INJECTION

6 mg

0.5 mL

For subcutaneous injection only.

Rx only

2 Single-Dose Syringe Cartridges

62000000090057 Rev. 10/23

PACKAGE LABEL

PRINCIPAL DISPLAY PANEL

NDC 0173-0479-00

IMITREX

STATdose SYSTEM

6 mg

This carton contains:

- Imitrex
(sumatriptan)
Injection

2 prefilled 0.5-mL syringe cartridges, each containing 6 mg of sumatriptan for subcutaneous injection only

- 1 Imitrex STATdose Pen
- 1 Carrying Case
- Instructions for Use/Information for the Patient
- Prescribing Information

This Product Contains Dry Natural Rubber

Rx only

Do not accept if security seal is missing or broken.

Made in India

©2023 the GSK group of companies or its licensor

62000000090058 Rev. 10/23